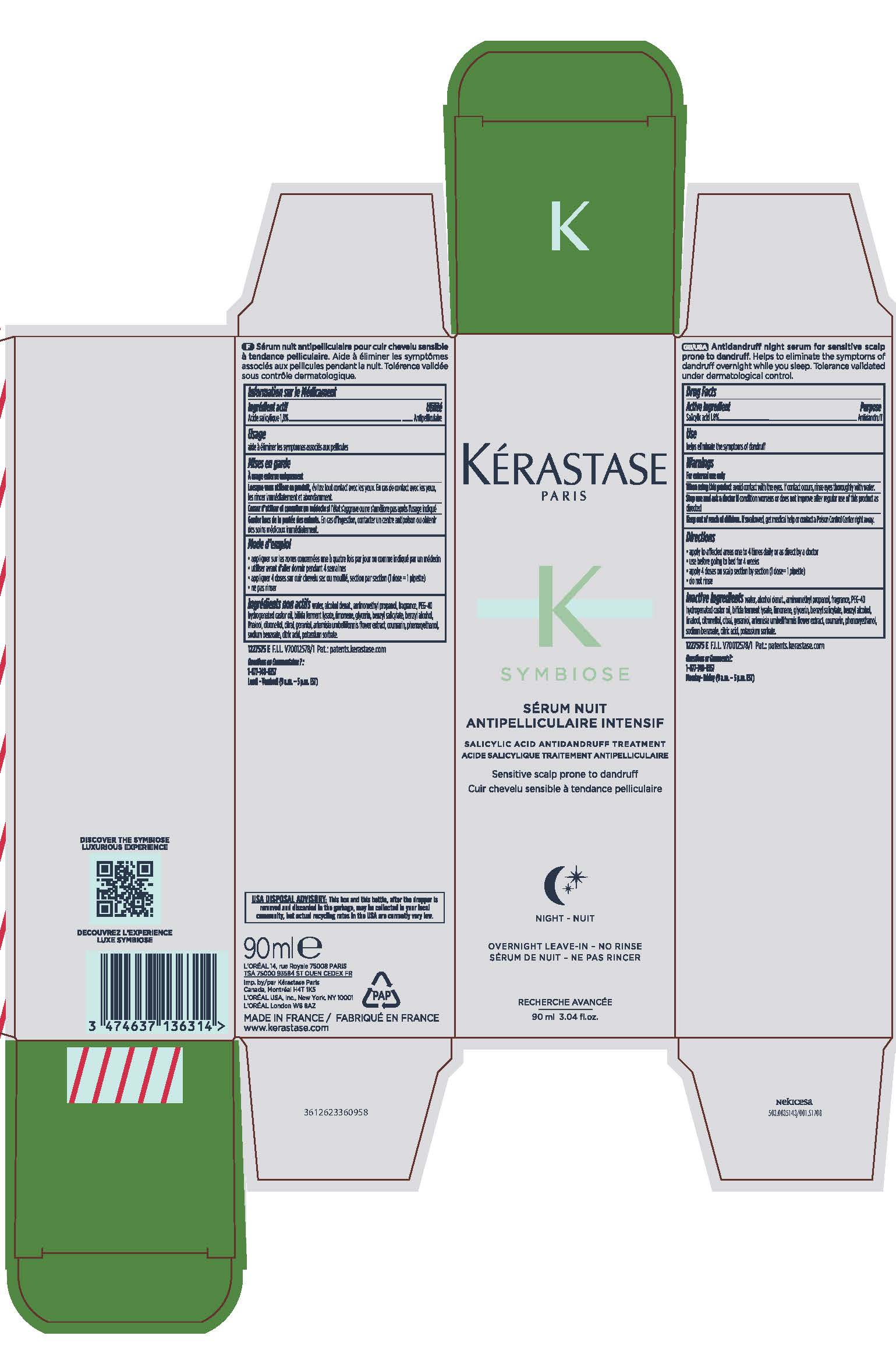 DRUG LABEL: Kerastase Paris K Symbiose Serum Nuit Antipelliculaire Intensif Antidandruff Treatment
NDC: 49967-363 | Form: LIQUID
Manufacturer: L'Oreal USA Products Inc.
Category: otc | Type: HUMAN OTC DRUG LABEL
Date: 20241230

ACTIVE INGREDIENTS: SALICYLIC ACID 18 mg/1 mL
INACTIVE INGREDIENTS: WATER; ALCOHOL; AMINOMETHYLPROPANOL; POLYOXYL 40 HYDROGENATED CASTOR OIL; LIMONENE, (+)-; GLYCERIN; BENZYL SALICYLATE; BENZYL ALCOHOL; LINALOOL, (+/-)-; .BETA.-CITRONELLOL, (R)-; CITRAL; GERANIOL; ARTEMISIA UMBELLIFORMIS FLOWER; COUMARIN; PHENOXYETHANOL; SODIUM BENZOATE; CITRIC ACID MONOHYDRATE; POTASSIUM SORBATE

Drug Facts

Active ingredient

Salicylic acid 1.8%

Purpose

Antidandruff

Use

- helps eliminate the symptoms of dandruff

Warnings

For external use only

When using this product

avoid contact with the eyes. If contact occurs, rinse eyes thoroughly with water.

Stop use and ask a doctor if

condition worsens or does not improve after regular use of this product as directed

Keep out of reach of children.

If swallowed, get medical help or contact a Poison Control Center right away.

Directions

- apply to affected areas one to 4 times daily or as directed by a doctor
- use before going to bed for 4 weeks
- apply 4 doses on scalp section by section (1 dose = 1 pipette)
- do not rinse

Inactive ingredients

water, alcohol denat., aminomethyl propanol, fragrance, PEG-40 hydrogenated castor oil, bifida ferment lysate, limonene, glycerin, benzyl salicylate, benzyl alcohol, linalool, citronellol, citral, geraniol, artemisia umbelliformis flower extract, coumarin, phenoxyethanol, sodium benzoate, citric acid, potassium sorbate